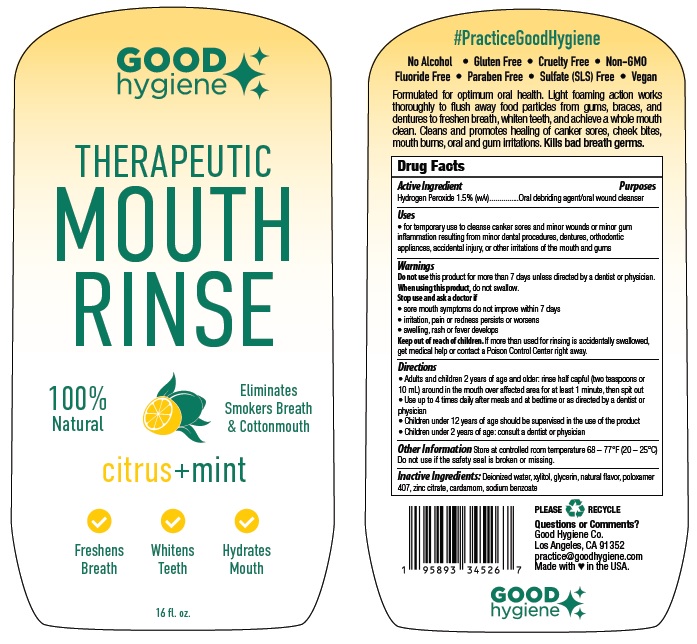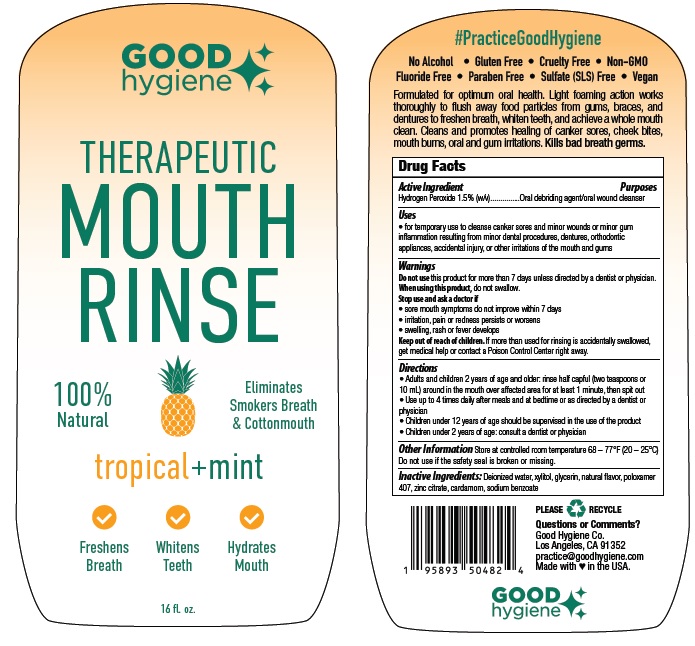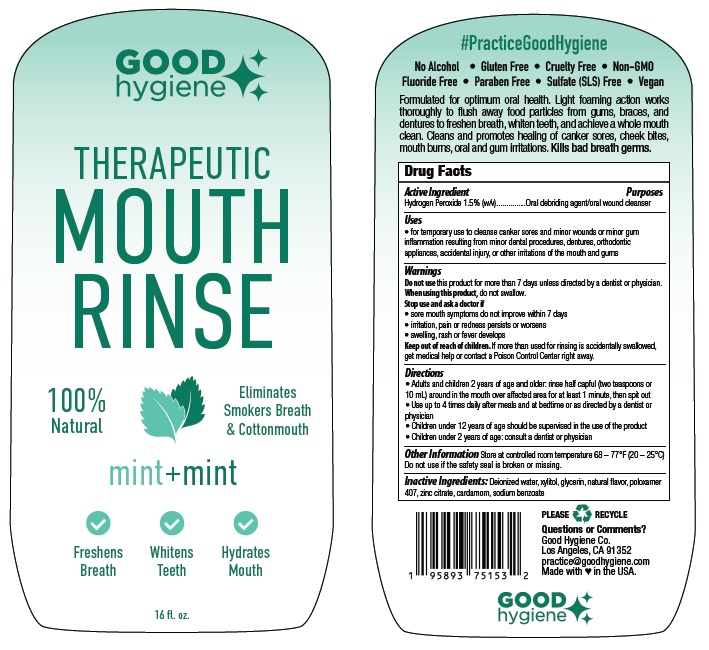 DRUG LABEL: Good Hygiene Therapeutic Mouth Rinse
NDC: 81439-100 | Form: LIQUID
Manufacturer: Good Hygiene Company
Category: otc | Type: HUMAN OTC DRUG LABEL
Date: 20230512

ACTIVE INGREDIENTS: HYDROGEN PEROXIDE 1.5 g/100 mL
INACTIVE INGREDIENTS: WATER; XYLITOL; GLYCERIN; POLOXAMER 407; ZINC CITRATE; CARDAMOM; SODIUM BENZOATE

Good Hygiene Therapeutic Mouth Rinse

Drug Facts

Active Ingredient
Hydrogen Peroxide 1.5% (w/v)

Purposes

Oral debriding agent/oral wound cleanser

Uses
• for temporary use to cleanse canker sores and minor wounds or minor gum
inflammation resulting from minor dental procedures, dentures, orthodontic
appliances, accidental injury, or other irritations of the mouth and gums

Warnings
Do not use this product for more than 7 days unless directed by a dentist or physician.
When using this product, do not swallow.
Stop use and ask a doctor if
• sore mouth symptoms do not improve within 7 days
• irritation, pain or redness persists or worsens
• swelling, rash or fever develops

Keep out of reach of children. If more than used for rinsing is accidentally swallowed,
get medical help or contact a Poison Control Center right away.

Directions
• Adults and children 2 years of age and older: rinse half capful (two teaspoons or
10 mL) around in the mouth over affected area for at least 1 minute, then spit out
• Use up to 4 times daily after meals and at bedtime or as directed by a dentist or
physician
• Children under 12 years of age should be supervised in the use of the product
• Children under 2 years of age: consult a dentist or physician

OTHER SAFETY INFORMATION

Other InformationStore at controlled room temperature 68 – 77°F (20 – 25°C)
Do not use if the safety seal is broken or missing.

INACTIVE INGREDIENT

Inactive Ingredients: Deionized water, xylitol, glycerin, natural flavor, poloxamer
407, zinc citrate, cardamom, sodium benzoate

Product Labeling

GOOD

hygiene

THERAPEUTIC
MOUTH
RINSE

mint + mint

Freshens Whitens Hydrates
Breath Teeth Mouth

16 fl. oz.

Good Hygiene Co.
Los Angeles, CA 91352
practice@goodhygiene.com
Made with ♥ in the USA.

Mint + Mint

Tropical + Mint

Citrus + Mint

res